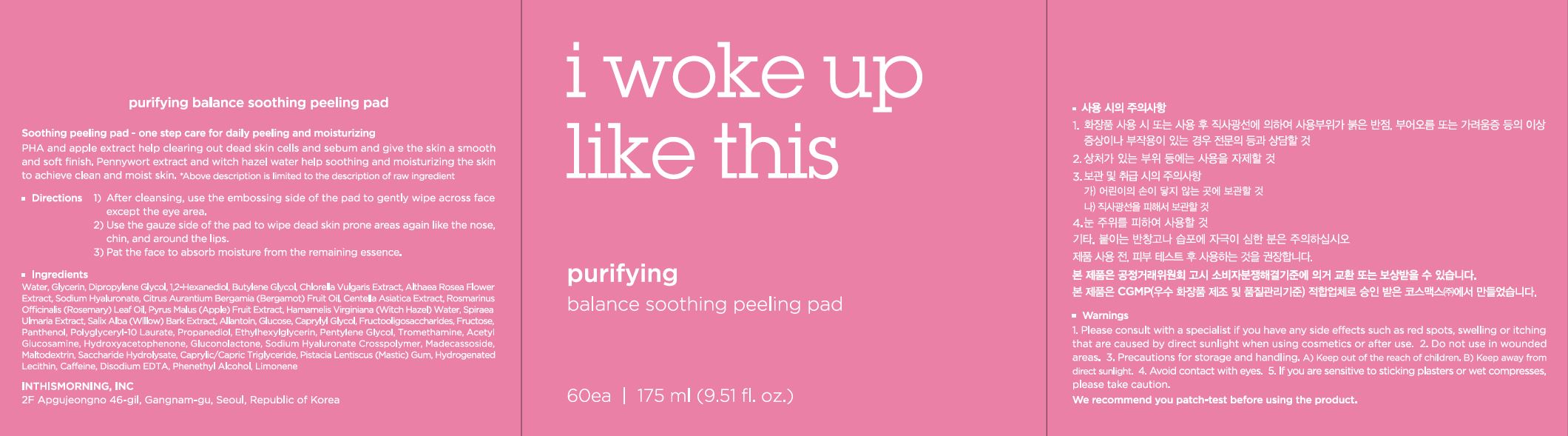 DRUG LABEL: Purifying Balance Soothing Peeling Pad
NDC: 71217-0055 | Form: LIQUID
Manufacturer: inthismorning co ltd
Category: otc | Type: HUMAN OTC DRUG LABEL
Date: 20230130

ACTIVE INGREDIENTS: LIMONENE, (+)- 0.00185573 g/100 mL
INACTIVE INGREDIENTS: GLYCERIN; WATER

Drug Facts

ACTIVE INGREDIENT

limonene

INACTIVE INGREDIENT

Water
Glycerin
Dipropylene Glycol
1,2-Hexanediol
Butylene Glycol
Allantoin
Caffeine
Chlorella Vulgaris Extract
Glucose
Caprylyl Glycol
Fructooligosaccharides
Fructose
Panthenol
Polyglyceryl-10 Laurate
Propanediol
Ethylhexylglycerin
Pentylene Glycol
Tromethamine
Disodium EDTA
Acetyl Glucosamine
Althaea Rosea Flower Extract
Sodium Hyaluronate
Citrus Aurantium Bergamia (Bergamot) Fruit Oil
Centella Asiatica Extract
Hydroxyacetophenone
Gluconolactone
Rosmarinus Officinalis (Rosemary) Leaf Oil
Sodium Hyaluronate Crosspolymer
Madecassoside
Pyrus Malus (Apple) Fruit Extract
Maltodextrin
Saccharide Hydrolysate
Hamamelis Virginiana (Witch Hazel) Water
Caprylic/Capric Triglyceride
Pistacia Lentiscus (Mastic) Gum
Hydrogenated Lecithin
Spiraea Ulmaria Extract
Phenethyl Alcohol
Salix Alba (Willow) Bark Extract

PURPOSE

skin peeling and moisturizing

keep out or reach of the children

INDICATIONS AND USAGE

after cleansing, use the embossing side of the pad to gently wipe across face except the eye area

use the gauze side of the pad to wipe dead skin prone areas again like the nose, chin, and around the lips

pat the fact to absorb moisture from the remaining essence

WARNINGS

This product is for exeternal use only. Do not use for internal use
Storage and handling precautions
If possible, avoid direct sunlight and store in cool and area of low humidity in order to maintain the quality of the product and avoid misuse
Avoid placing the product near fire and store out in reach of children

- consult a physician in case of abnormal symptoms, such as red spots, swelling or itching, or side effects in the areas of application due to direct light during or after using the product

- do not use on wounded area

DOSAGE AND ADMINISTRATION

for external use only